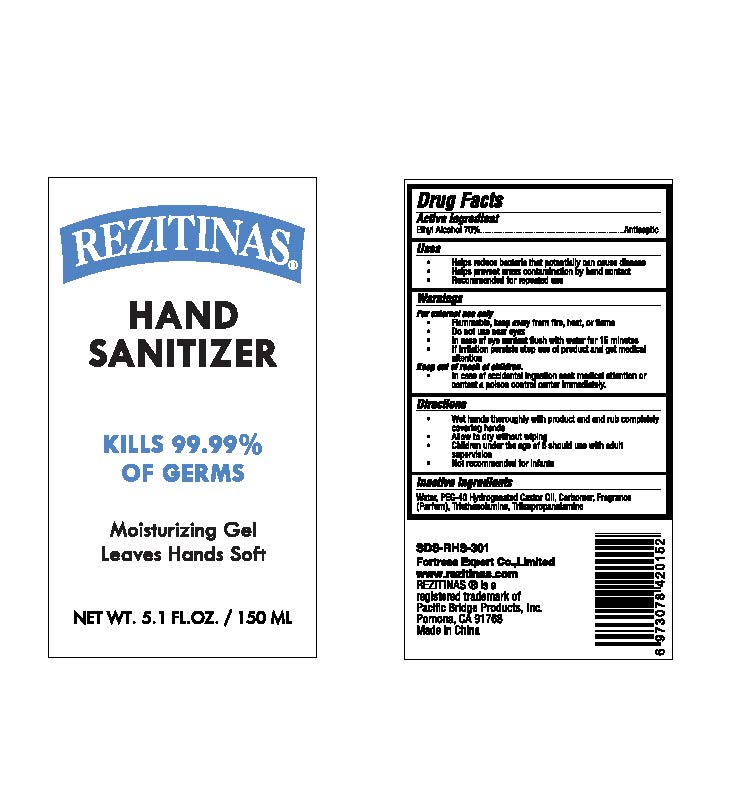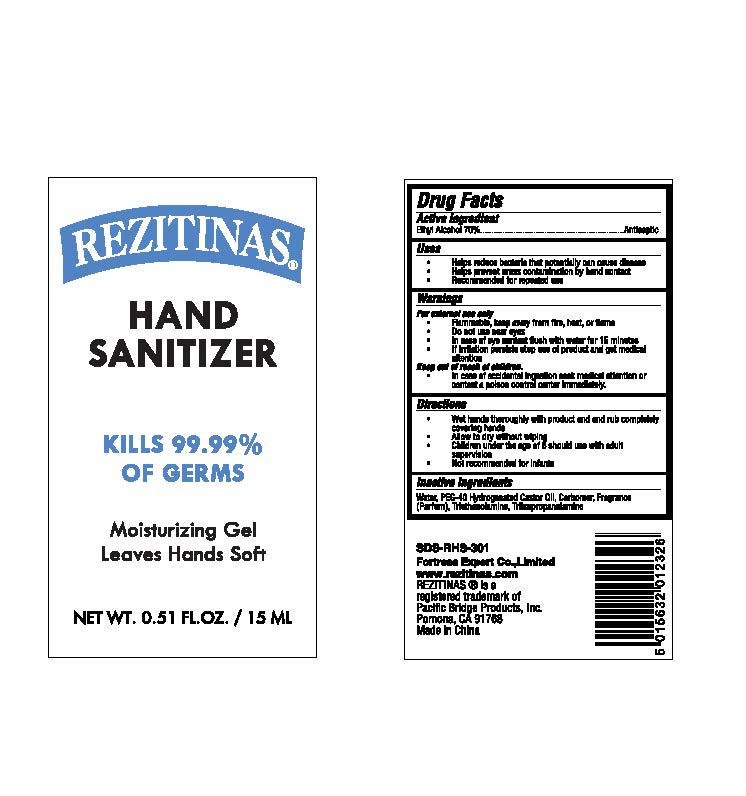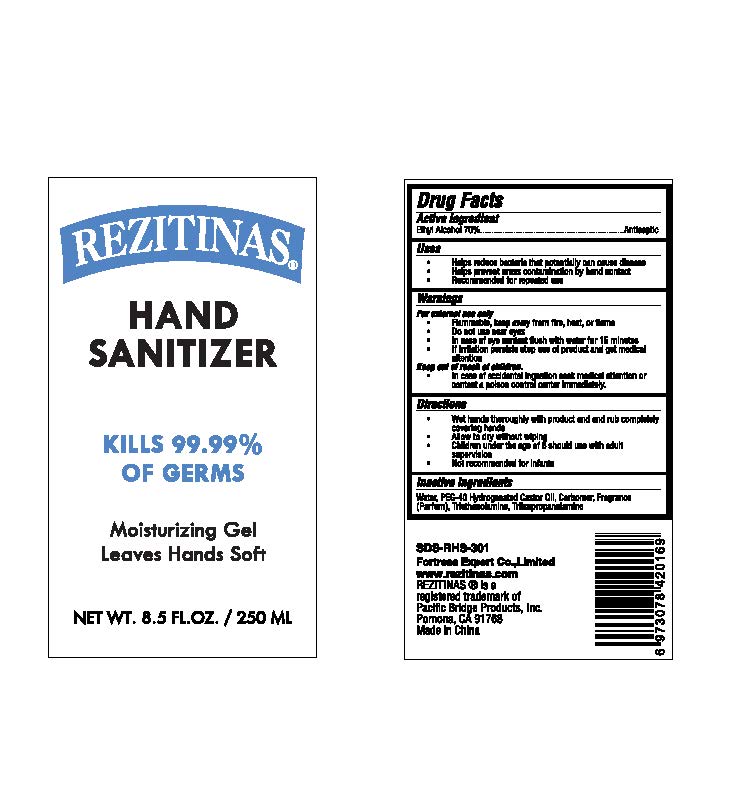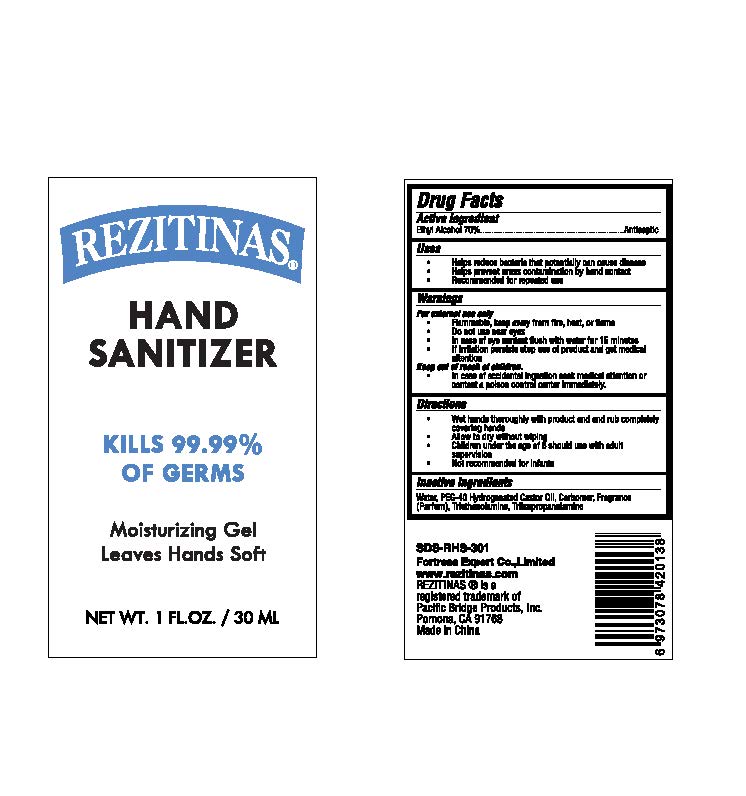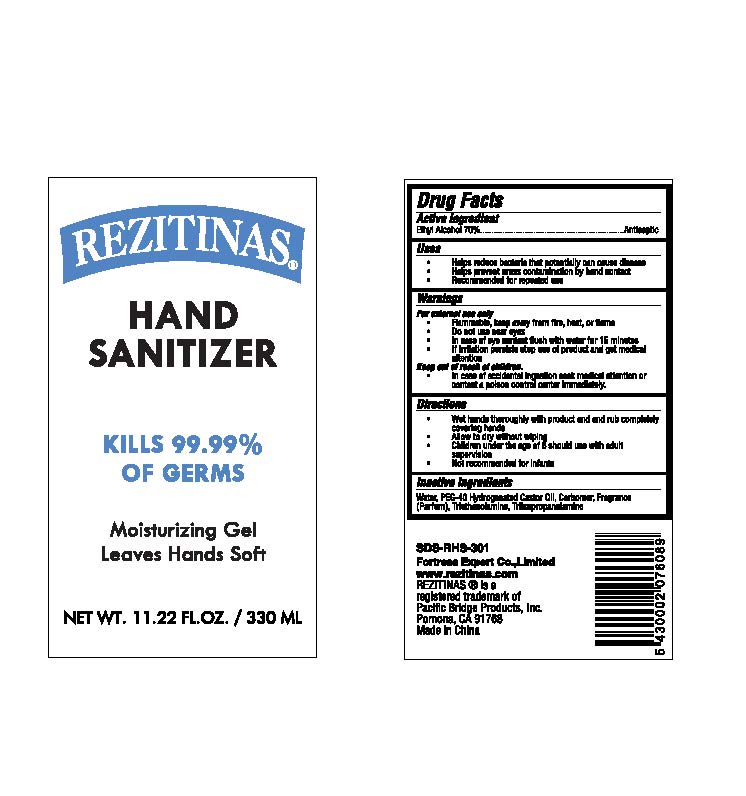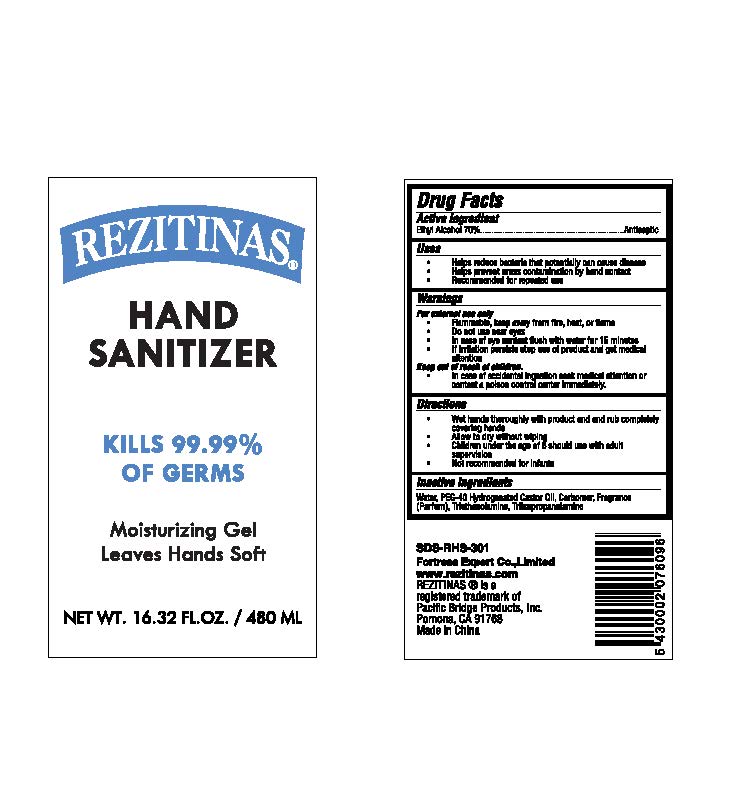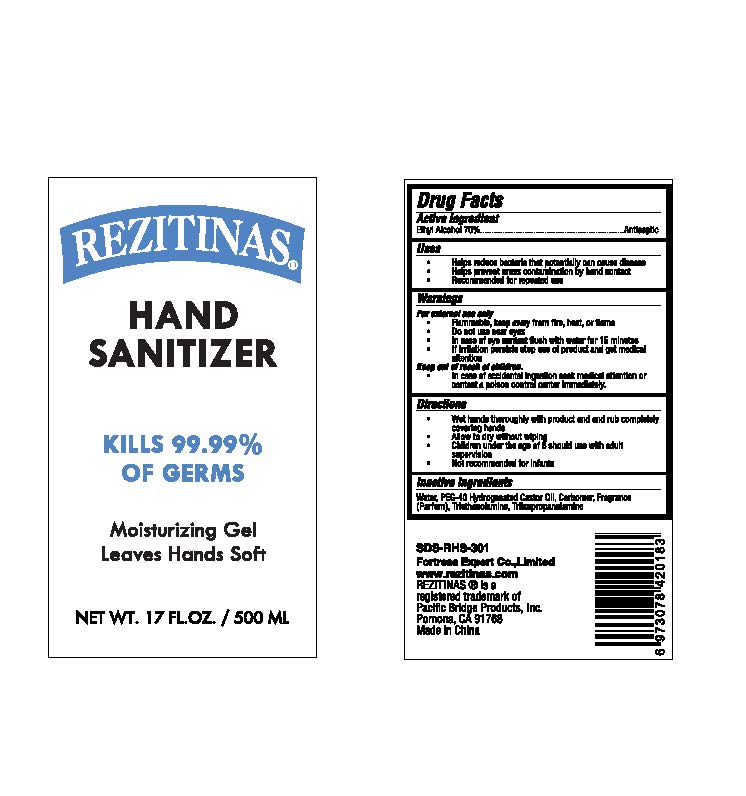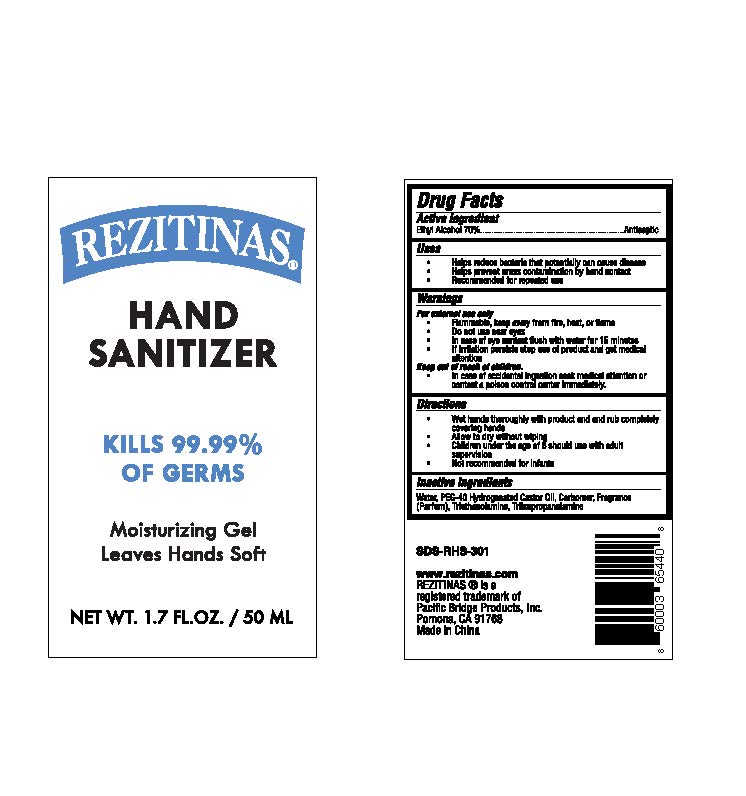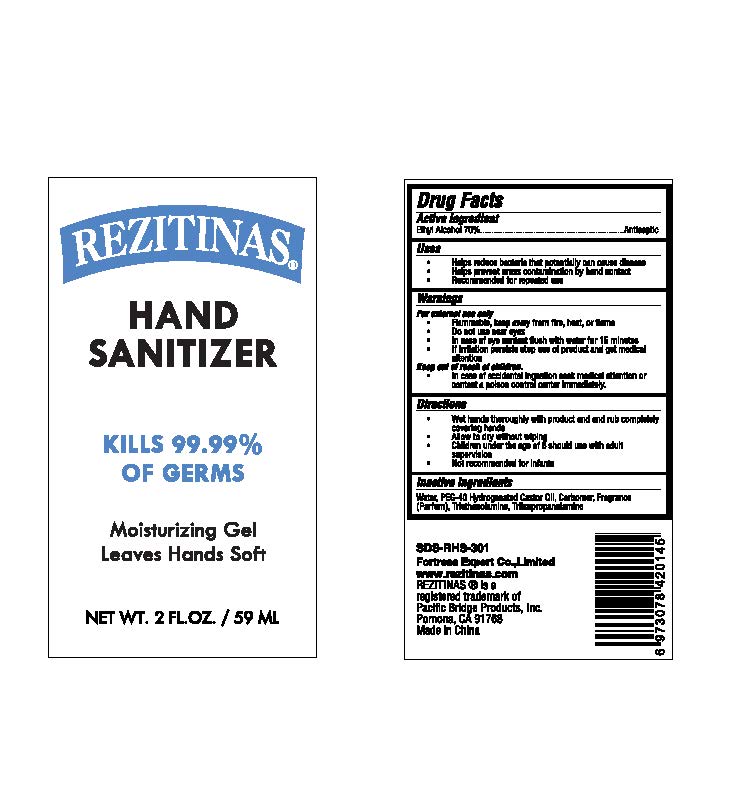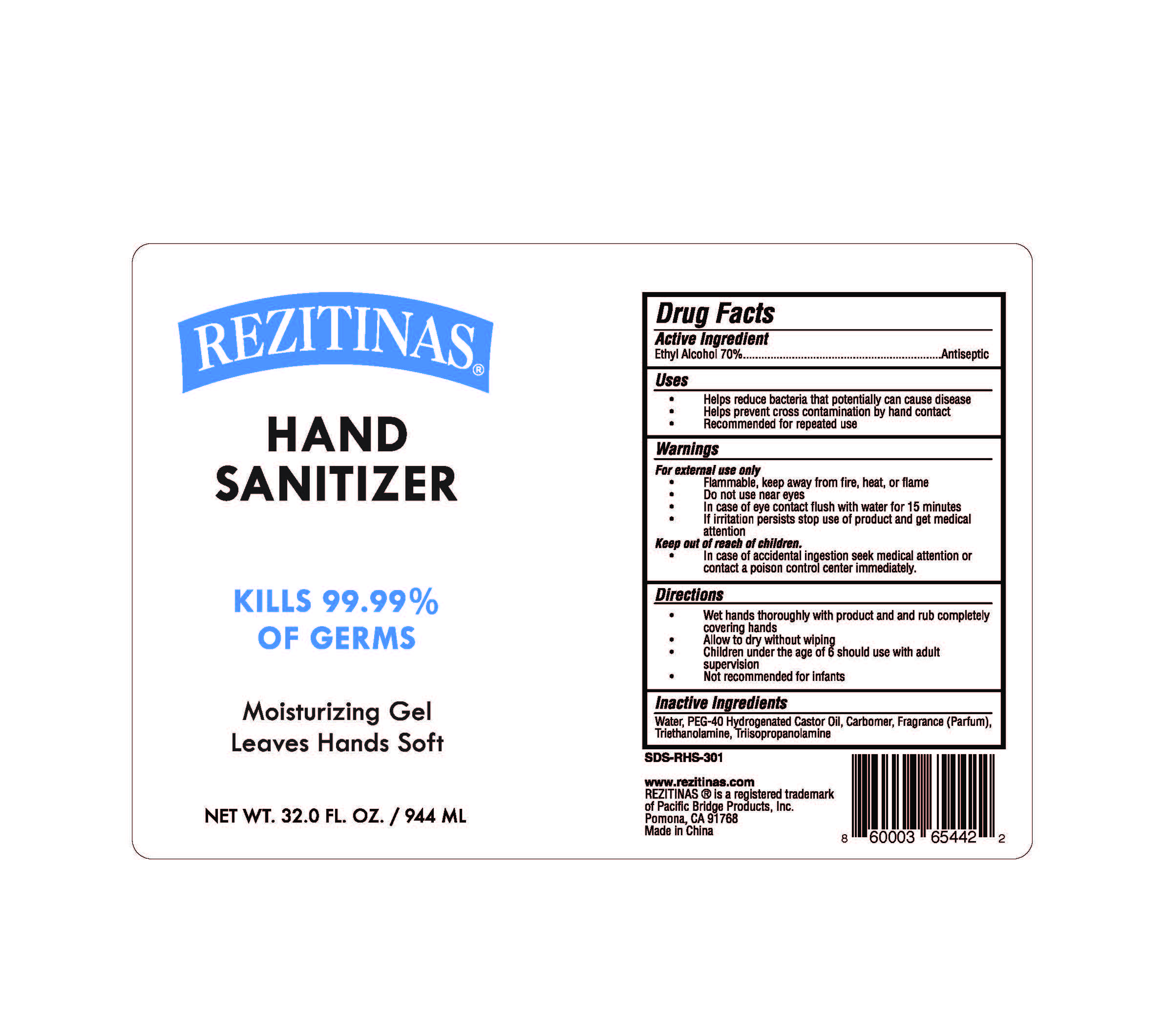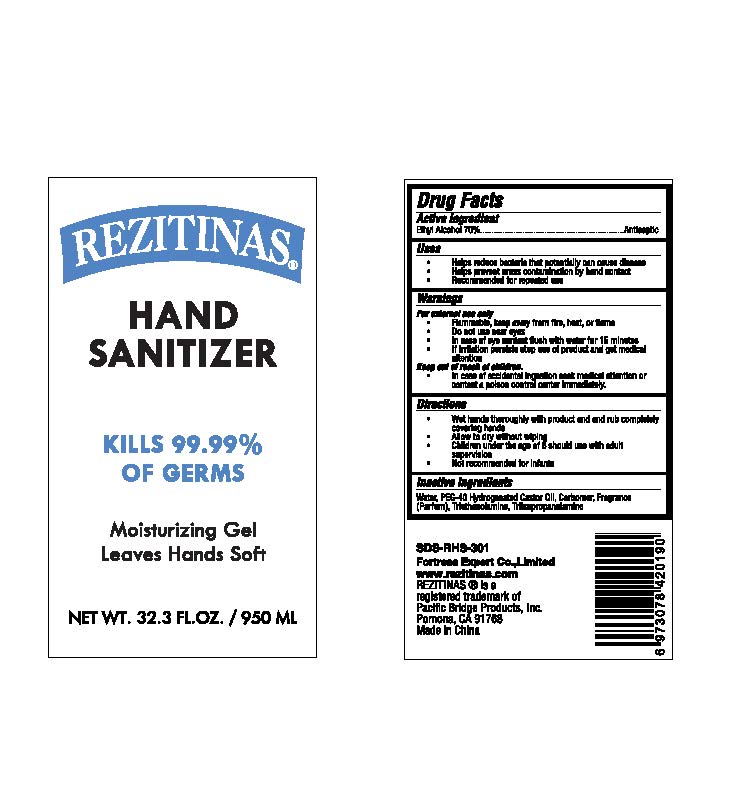 DRUG LABEL: Hand Sanitizer
NDC: 73549-001 | Form: GEL
Manufacturer: Fortress Expert Co., Ltd
Category: otc | Type: HUMAN OTC DRUG LABEL
Date: 20200408

ACTIVE INGREDIENTS: ALCOHOL 70 mL/100 mL
INACTIVE INGREDIENTS: TRIISOPROPANOLAMINE; TRIETHANOLAMINE LAURYL SULFATE; POLYOXYL 40 HYDROGENATED CASTOR OIL; CARBOMER 940; WATER

Active Ingredient(s)

Alcohol 70% v/v. Purpose: Antiseptic

Purpose

Antiseptic, Hand Sanitizer

Use

Helps reduce bacteria that potentially can cause disease

Helps prevent Cross contamination by hand contact

Recommended for repeated use

Warnings

For external use only.

Flammable. Keep away from fire heat, or flame

Do not use near eyes

Incase of eye contact flush with water for 15 minutes

If irritation persists stop use of product and get medical attention

Do not use

- in children less than 2 months of age
- on open skin wounds

When using this product keep out of eyes, ears, and mouth. In case of contact with eyes, rinse eyes thoroughly with water.
Stop use and ask a doctor if irritation or rash occurs. These may be signs of a serious condition.
Keep out of reach of children. If swallowed, get medical help or contact a Poison Control Center right away.

Stop use and ask a doctor if irritation or rash occurs. These may be signs of a serious condition.

Keep out of reach of children.

In case of accidental ingestion seek medical attention or contact a poison control center immediately

Directions

Wet hands thoroughly with product andand rub completelycovering hands

Allow to dry without wiping

Children under the age of 6 should use with adultsupervision

Not recommended for infants

Other information

Avoid freezing and excessive heat above 40C (104F)

Inactive ingredients

Water, PEG-40 Hydrogenated Castor Oil, Carbomer, FragranceParfum), Triethanolamine, Triisopropanolamine